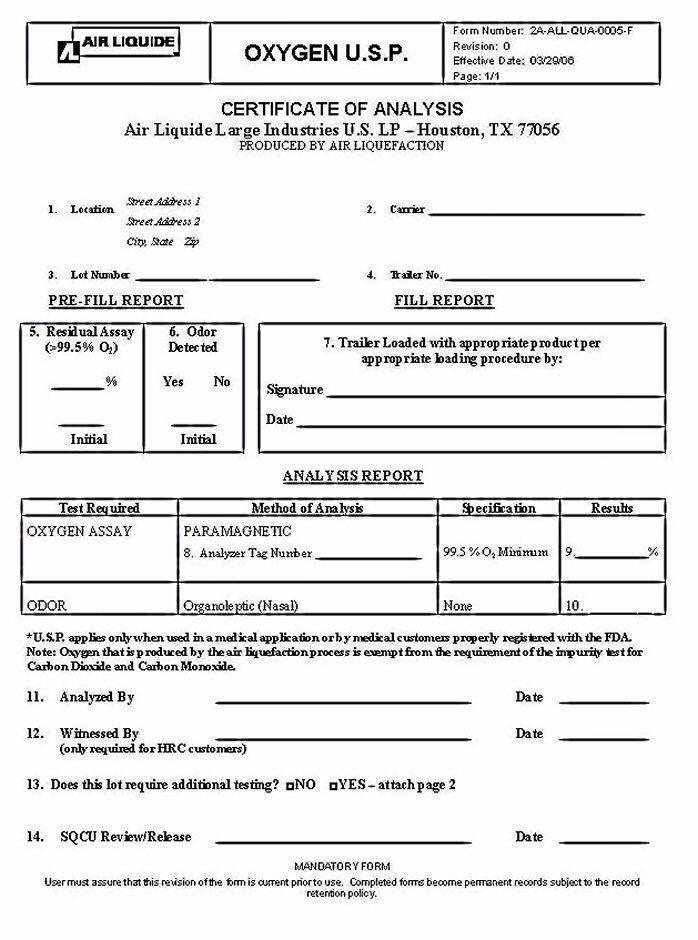 DRUG LABEL: OXYGEN
NDC: 11853-013 | Form: GAS
Manufacturer: Air Liquide Large Industries U.S. LP
Category: prescription | Type: HUMAN PRESCRIPTION DRUG LABEL
Date: 20250116

ACTIVE INGREDIENTS: OXYGEN 99 L/100 L

Oxygen USP Bulk Liquid

Oxygen USP COA

AIR LIQUIDE OXYGEN U.S.P. Form Number: 2A-ALL-QUA-0005-F

Revision: 0

Effective Date: 03/29/06

Page: 1/1

CERTIFICATE OF ANALYSIS

Air Liquide large Industries U.S. L.P. – Houston, TX 77056

PRODUCED BY AIR LIQUEFACTION

1.Location Street Address1 2. Carrier ________________

Street Address 2

City, State Zip

3. Lot Number ______________________ 4. Trailer No _____________

PRE-FILL REPORT FILL REPORT

5.Residual Assay 6. Odor 7. Trailer loaded with appropriate product per appropriate

(>99.5% O2) Detected loading procedure by:

_______ % Yes No Signature _________________________

________ ________ Date _____________________________

Initial Initial

ANALYSIS REPORT

Test required Method of Analysis Specifications Results

OXYGEN ASSAY PARAMAGNETIC ___ 99.5% O2 Minimum 9. ____%

8.Analyzer Tag Number

ODOR Organoleptic (Nasal) None 10. ______

USP applies only when used in a medical application or by medical customers properly registered with the FDA. Note: Oxygen that is produced by the air liquefaction process is exempt from the requirement of the impurity test for Carbon Dioxide and Carbon Monoxide.

11. Analyzed By ________________________ Date ____________

12. Witnessed By ________________________ Date ____________

(only required for HRC customers)

13. Does this lot require additional testing? ___ NO ___ YES – attach page 2

14. SQCU Review/Release _______________________ Date ____________

MANDATORY FORM

User must assure that this revision of the form is current prior to use. Completed forms become permanent records subject to the record retention policy.